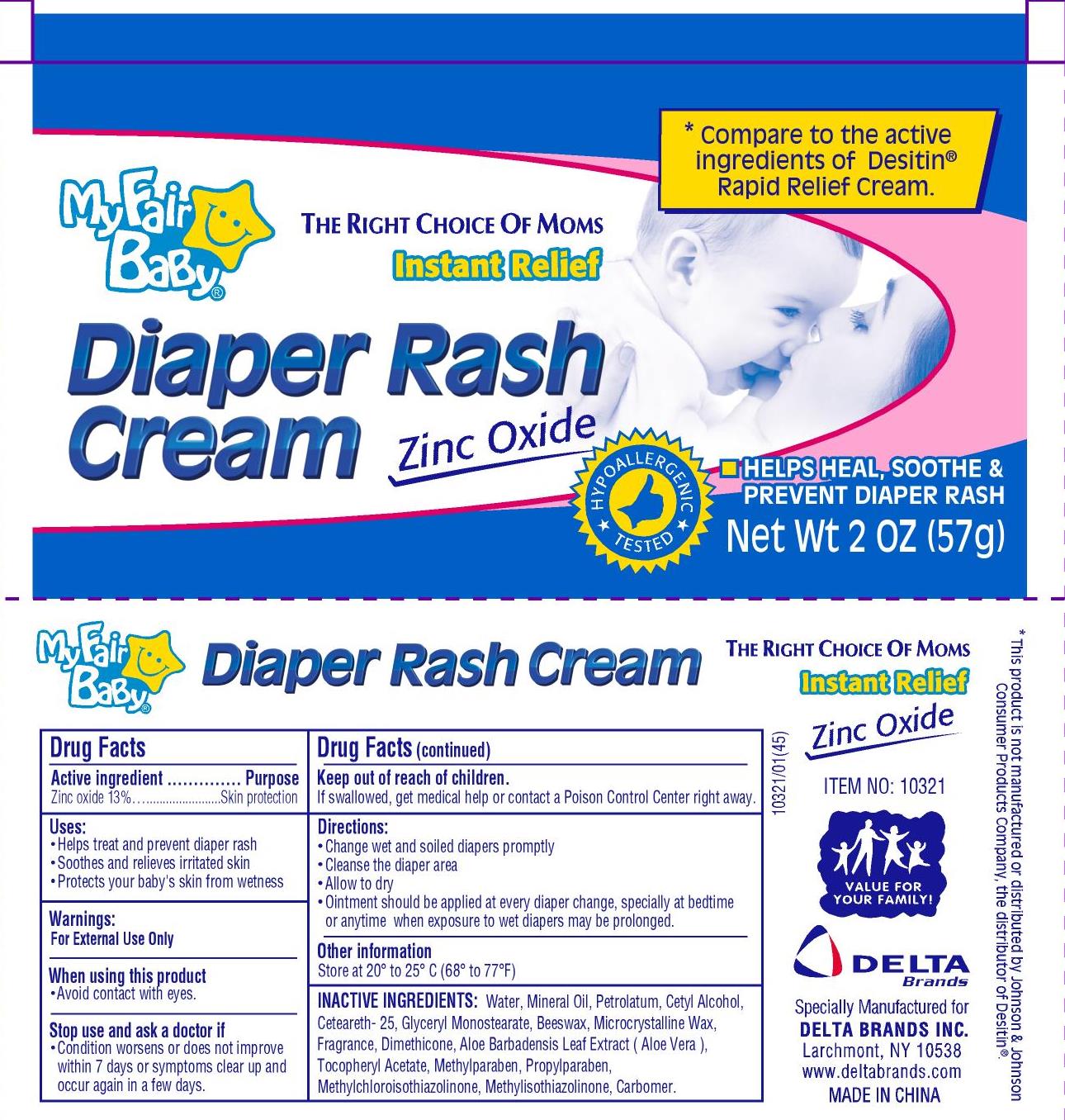 DRUG LABEL: My Fair Baby
NDC: 47046-179 | Form: CREAM
Manufacturer: Anicare Pharmaceuticals Pvt. Ltd.
Category: otc | Type: HUMAN OTC DRUG LABEL
Date: 20201220

ACTIVE INGREDIENTS: ZINC OXIDE 13 g/100 g
INACTIVE INGREDIENTS: WATER; MINERAL OIL; PETROLATUM; CETYL ALCOHOL; CETEARETH-25; GLYCERYL MONOSTEARATE; WHITE WAX; MICROCRYSTALLINE WAX; DIMETHICONE; ALOE VERA LEAF; METHYLPARABEN; PROPYLPARABEN; METHYLCHLOROISOTHIAZOLINONE; METHYLISOTHIAZOLINONE

diaper rash cream

Active Ingredient

Zinc Oxide 13%

Purpose

Skin Protection

Use

- Helps treat and prevent diaper rash
- Soothes and relieves irritated skin
- Protects your baby's skin from wetness

Warnings

For external use only

When using this product

Avoid contact with the eyes

Stop use and ask a doctor if

Condition worsens or does not improve within 7 days or symptoms clear up and occur again within a few days.

Keep out of reach of children

If swallowed, get medical help or contact a Poison Control Center right away

Directions

- Change wet and soiled diapers promptly
- Cleanse the diaper area
- Allow to dry
- Ointment should be applied at every diaper change, specially at bedtime or anytime when exposure to wet diapers may be prolonged

Other Information

Store at 20º to 25°C (68° to 77°F)

Inactive Ingredients

Water, Mineral Oil, Petrolatum, Cetyl Alcohol, Ceteareth-25, Glyceryl Monostearate, Beeswax, Microcrystaline Wax, Fragrance, Dimethicone, Aloe Barbadensis Leaf Extract (Aloe Vera), Tocopheryl Acetate, Methylparaben, Propylparaben, Methylchloroisothiazolinone, Methylisothiazolinone, Carbomer